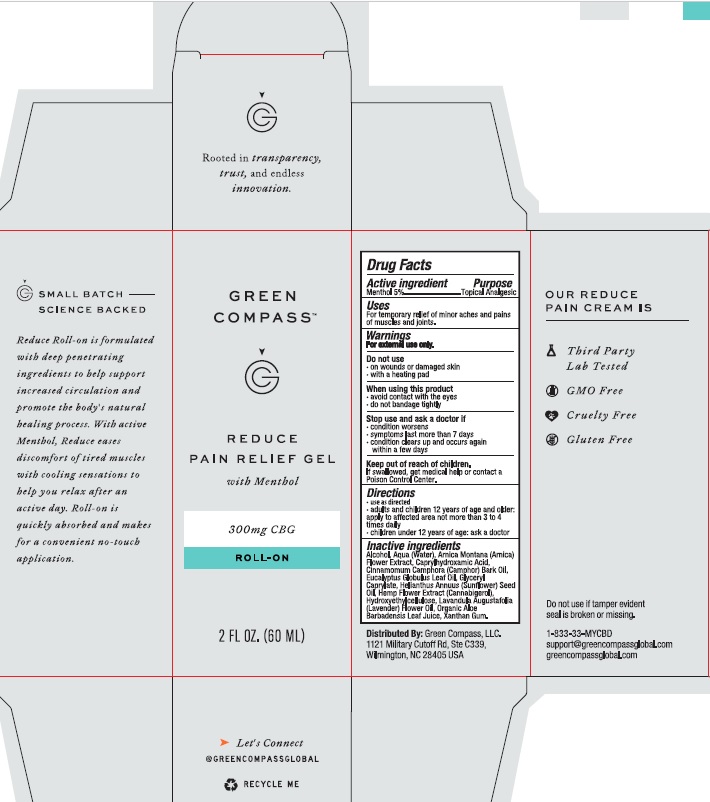 DRUG LABEL: Green Compass Reduce Pain Relief with Menthol
NDC: 73132-005 | Form: GEL
Manufacturer: Green Compass, Inc.
Category: otc | Type: HUMAN OTC DRUG LABEL
Date: 20250101

ACTIVE INGREDIENTS: MENTHOL, UNSPECIFIED FORM 5 g/100 mL
INACTIVE INGREDIENTS: XANTHAN GUM; ARNICA MONTANA; HYDROXYETHYL CELLULOSE, UNSPECIFIED; CANNABIGEROL; SUNFLOWER OIL; GLYCERYL CAPRYLATE; ALCOHOL; CAPRYLHYDROXAMIC ACID; ALOE VERA LEAF; EUCALYPTUS OIL; LAVENDER OIL; WATER; CAMPHOR OIL

Green Compass Reduce Pain Relief Gel with Menthol

Drug Facts

Active ingredient

Menthol 5%

Purpose

Topical Analgesic

Uses

For temporary relief of minor aches and pains of muscles and joints.

Warnings

For external use only.

Do not use

- on wounds or damaged skin
- with a heating pad

When using this product

- avoid contact with the eyes
- do not bandage tightly

Stop use and ask a doctor if

- condition worsens
- symptoms last more than 7 days
- condition clears up and occurs again within a few days

Keep out of reach of children. If swallowed, get medical help or contact a Poison Control Center.

Directions

- use as directed
- adults and children 12 years of age and older: apply to affected area not more than 3 to 4 times daily
- children under 12 years of age: ask a doctor

Inactive ingredients

Alcohol, aqua (water), arnica montana (arnica) flower extract, Caprylhydroxamic Acid, Cinnamomum Camphora (Camphor) Bark Oil, eucalyptus globulus leaf oil, glyceryl caprylate, helianthus annuus (sunflower) seed oil, hemp flower extract (cannabigerol), hydroxyethylcellulose, lavandula angustifolia (lavender) flower oil, organic aloe barbadensis leaf juice, xanthan gum.

Distributed By:

Green Compass, LLC.

1121 Military Cutoff Rd., Ste C339

Wilmington, NC 28405 USA

Do not use if tamper evident seal is broken or missing.

1-833-33-MYCBD

support@greencompassglobal.com

greencompassglobal.com

PACKAGE LABEL

GREEN COMPASS

REDUCE

PAIN RELIEF GEL

with Menthol

300 mg CBG

ROLL-ON

2 FL OZ (60 mL)